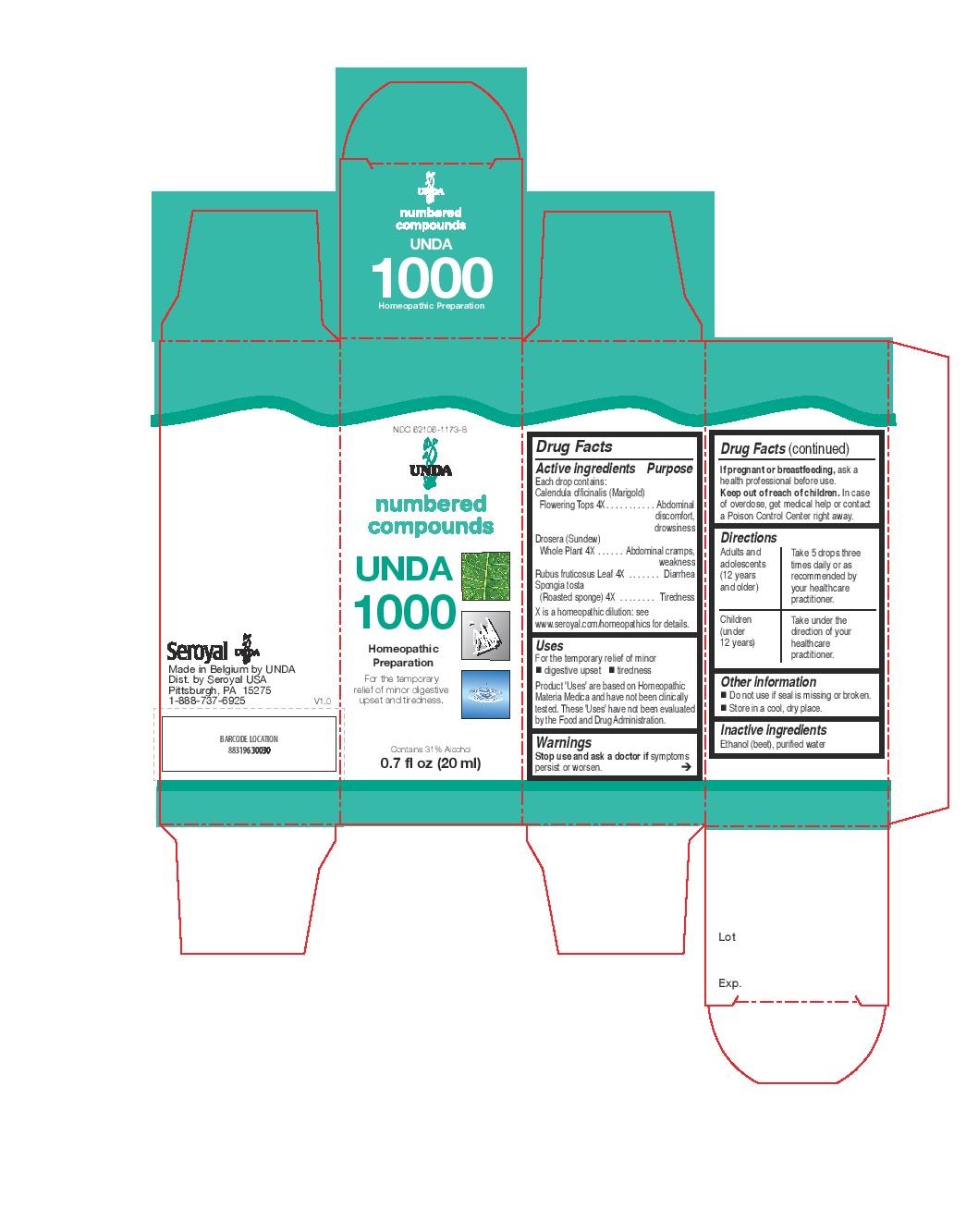 DRUG LABEL: UNDA 1000
NDC: 62106-1173 | Form: LIQUID
Manufacturer: Seroyal USA
Category: homeopathic | Type: HUMAN OTC DRUG LABEL
Date: 20221109

ACTIVE INGREDIENTS: RUBUS FRUTICOSUS LEAF 4 [hp_X]/20 mL; CALENDULA OFFICINALIS FLOWERING TOP 4 [hp_X]/20 mL; DROSERA ROTUNDIFOLIA FLOWERING TOP 4 [hp_X]/20 mL; SPONGIA OFFICINALIS SKELETON, ROASTED 4 [hp_X]/20 mL
INACTIVE INGREDIENTS: ALCOHOL; WATER

UNDA 1000

Active ingredients
Calendula officinalis (Marigold) Flowering Tops 4X
Drosera (Sundew) Whole Plant 4X
Rubus fruticosus Leaf 4X
Spongia tosta (Roasted sponge) 4X

Uses

For the temporary relief of minor digestive upset and tiredness.

Warnings

Stop use and ask a doctor if symptoms persist or worsen.
If pregnant or breastfeeding, ask a health professional before use.

Keep out of reach of children.

In case of overdose, get medical help or contact a Poison Control Center right away.

PREGNANCY OR BREAST FEEDING

If pregnant or breastfeeding, ask a health professional before use.

Keep out of reach of children.

OVERDOSAGE

In case of overdose, get medical help or contact a Poison Control Center right away.

Stop use and ask a doctor if symptoms persist or worsen.

Inactive ingredients
Ethanol (beet), purified water

Other information
Do not use if seal is missing or broken.
Store in a cool, dry place.

Directions
Adults and adolescents (12 years and older)

Take 5 drops three times daily or as recommended by your healthcare practitioner.
Children (under 12 years)
Take under the direction of your healthcare practitioner.

Uses
For the temporary relief of minor digestive upset and tiredness.

Directions
Adults and adolescents (12 years and older)

Take 5 drops three times daily or as recommended by your healthcare practitioner.
Children (under 12 years)
Take under the direction of your healthcare practitioner.

PACKAGE LABEL

NDC 62106-1173-8

UNDA
numbered compounds
UNDA 1000
Homeopathic Preparation

For the temporary relief of minor

digestive upset and tiredness.
Contains 31% Alcohol
0.7 fl oz (20 ml)